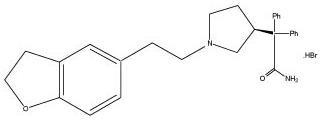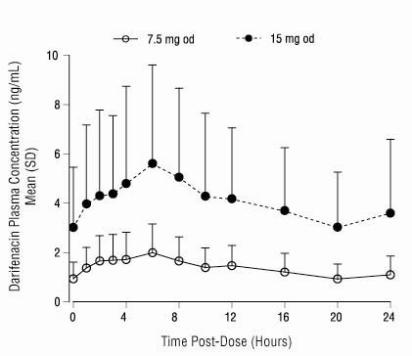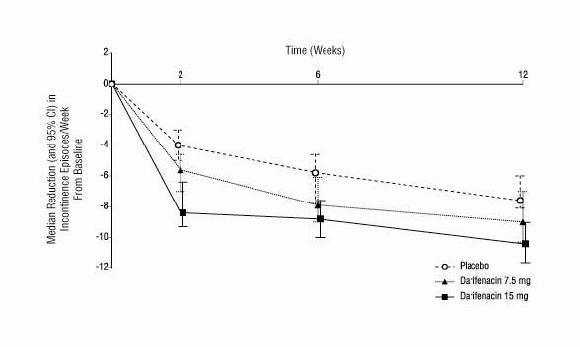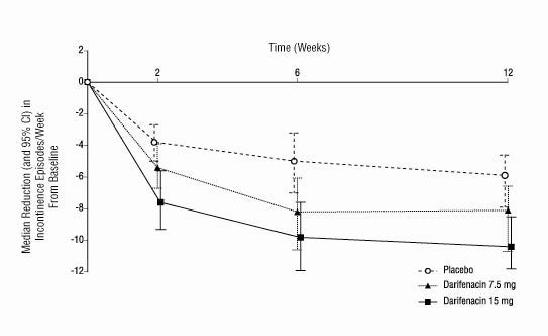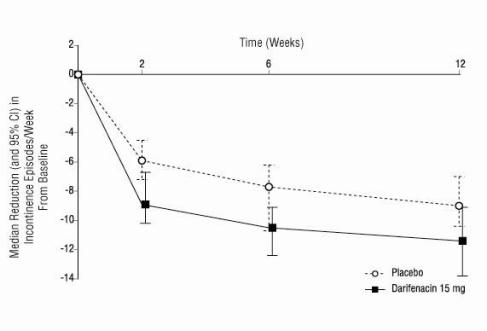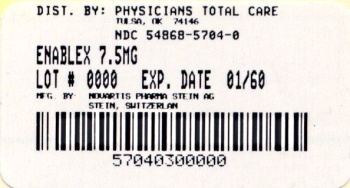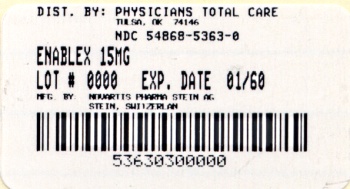 DRUG LABEL: Enablex
NDC: 54868-5704 | Form: TABLET, EXTENDED RELEASE
Manufacturer: Physicians Total Care, Inc.
Category: prescription | Type: HUMAN PRESCRIPTION DRUG LABEL
Date: 20100101

ACTIVE INGREDIENTS: DARIFENACIN 7.5 mg/1 1
INACTIVE INGREDIENTS: ANHYDROUS DIBASIC CALCIUM PHOSPHATE; HYPROMELLOSE; POLYETHYLENE GLYCOL; MAGNESIUM STEARATE; TITANIUM DIOXIDE; TALC

ENABLEX®
(darifenacin)
Extended-release tablets
Rx only
Prescribing Information

DESCRIPTION

ENABLEX® (darifenacin) is an extended-release tablet which contains 7.5 mg or 15 mg darifenacin as its hydrobromide salt. The active moiety, darifenacin, is a potent muscarinic receptor antagonist.

Chemically, darifenacin hydrobromide is (S)-2-{1-[2-(2,3-dihydrobenzofuran-5-yl)ethyl]-3-pyrrolidinyl}-2,2-diphenylacetamide hydrobromide. The empirical formula of darifenacin hydrobromide is C28H30N2O2.HBr.

The structural formula is

Darifenacin hydrobromide is a white to almost white, crystalline powder, with a molecular weight of 507.5.

ENABLEX is a once a day extended release tablet and contains the following inactive ingredients: dibasic calcium phosphate, hypromellose (hydroxypropyl methylcellulose), magnesium stearate, polyethylene glycol, talc, titanium dioxide. The 15-mg tablet also contains iron oxide red and iron oxide yellow.

CLINICAL PHARMACOLOGY

General

Darifenacin is a competitive muscarinic receptor antagonist. Muscarinic receptors play an important role in several major cholinergically mediated functions, including contractions of the urinary bladder smooth muscle and stimulation of salivary secretion.

In vitro studies using human recombinant muscarinic receptor subtypes show that darifenacin has greater affinity for the M3 receptor than for the other known muscarinic receptors (9- and 12-fold greater affinity for M3 compared to M1 and M5, respectively, and 59-fold greater affinity for M3 compared to both M2 and M4). M3 receptors are involved in contraction of human bladder and gastrointestinal smooth muscle, saliva production, and iris sphincter function. Adverse drug effects such as dry mouth, constipation and abnormal vision may be mediated through effects on M3 receptors in these organs.

Pharmacodynamics

In three cystometric studies performed in patients with involuntary detrusor contractions, increased bladder capacity was demonstrated by an increased volume threshold for unstable contractions and diminished frequency of unstable detrusor contractions after ENABLEX® (darifenacin) extended-release tablet treatment. These findings are consistent with an antimuscarinic action on the urinary bladder.

Pharmacokinetics

Absorption

After oral administration of ENABLEX to healthy volunteers, peak plasma concentrations of darifenacin are reached approximately seven hours after multiple dosing and steady-state plasma concentrations are achieved by the sixth day of dosing. The mean (SD) steady-state time course of ENABLEX 7.5 mg and 15 mg extended-release tablets is depicted in Figure 1.

Figure 1 Mean (SD) Steady-State Darifenacin Plasma Concentration-Time Profiles for ENABLEX® 7.5 mg and 15 mg in Healthy Volunteers Including Both CYP2D6 EMs and PMs*

*Includes 95 EMs and 6 PMs for 7.5 mg; 104 EMs and 10 PMs for 15 mg.

A summary of mean (standard deviation, SD) steady-state pharmacokinetic parameters of ENABLEX 7.5 mg and 15 mg extended-release tablets in extensive (EMs) and poor (PMs) metabolizers of CYP2D6 is provided in Table 1.

Table 1: Mean (SD) Steady-State Pharmacokinetic Parameters from ENABLEX® 7.5 mg and 15 mg Extended-Release Tablets Based on Pooled Data by Predicted CYP2D6 Phenotype
 | ENABLEX® 7.5 mg (N = 68 EM, 5 PM) |  |  |  |  | ENABLEX® 15 mg (N = 102 EM, 17 PM)
 | AUC 24 (ng.h/mL) | Cmax (ng/mL) | Cavg (ng/mL) | Tmax (h) | t 1/2 (h) | AUC 24 (ng.h/mL) | Cmax (ng/mL) | Cavg (ng/mL) | Tmax (h) | t 1/2 (h)
EM | 29.24 (15.47) | 2.01 (1.04) | 1.22 (0.64) | 6.49 (4.19) | 12.43 (5.64) a | 88.90 (67.87) | 5.76 (4.24) | 3.70 (2.83) | 7.61 (5.06) | 12.05 (12.37) b
PM | 67.56 (13.13) | 4.27 (0.98) | 2.81 (0.55) | 5.20 (1.79) | 19.95c - | 157.71 (77.08) | 9.99 (5.09) | 6.58 (3.22) | 6.71 (3.58) | 7.40d -
a N=25; b N=8; c N=2; d N=1; AUC24 = Area under the plasma concentration versus time curve for 24h;
Cmax = Maximum observed plasma concentration; Cavg = Average plasma concentration at steady state;
Tmax = Time of occurrence of Cmax; t1/2 = Terminal elimination half-life. Regarding EM and PM, see CLINICAL PHARMACOLOGY, Pharmacokinetics, Variability in Metabolism.

The mean oral bioavailability of ENABLEX in EMs at steady state is estimated to be 15% and 19% for 7.5-mg and 15-mg tablets, respectively.

Effect of Food

There is no effect of food on multiple-dose pharmacokinetics from ENABLEX extended-release tablets.

Distribution

Darifenacin is approximately 98% bound to plasma proteins (primarily to alpha-1-acid-glycoprotein). The steady-state volume of distribution (Vss) is estimated to be 163 L.

Metabolism

Darifenacin is extensively metabolized by the liver following oral dosing.

Metabolism is mediated by cytochrome P450 enzymes CYP2D6 and CYP3A4. The three main metabolic routes are as follows:

1. monohydroxylation in the dihydrobenzofuran ring;
2. dihydrobenzofuran ring opening;
3. N-dealkylation of the pyrrolidine nitrogen.

The initial products of the hydroxylation and N-dealkylation pathways are the major circulating metabolites but they are unlikely to contribute significantly to the overall clinical effect of darifenacin.

Variability in Metabolism

A subset of individuals (approximately 7% Caucasians and 2% African Americans) are poor metabolizers (PMs) of CYP2D6 metabolized drugs. Individuals with normal CYP2D6 activity are referred to as extensive metabolizers (EMs). The metabolism of darifenacin in PMs will be principally mediated via CYP3A4. The darifenacin ratios (PM:EM) for Cmax and AUC following darifenacin 15 mg once-daily at steady state were 1.9 and 1.7, respectively.

Excretion

Following administration of an oral dose of ^14C-darifenacin solution to healthy volunteers, approximately 60% of the radioactivity was recovered in the urine and 40% in the feces. Only a small percentage of the excreted dose was unchanged darifenacin (3%). Estimated darifenacin clearance is 40 L/h for EMs and 32 L/h for PMs. The elimination half-life of darifenacin following chronic dosing is approximately 13-19 hours.

Pharmacokinetics in Special Populations

Age: No dose adjustment is recommended for the elderly.

A population pharmacokinetic analysis of patient data indicated a trend for clearance of darifenacin to decrease with age (6% per decade relative to a median age of 44). Following administration of ENABLEX 15 mg once-daily, darifenacin exposure at steady state was approximately 12%-19% higher in volunteers between 45 and 65 years of age compared to younger volunteers aged 18 to 44 years (see PRECAUTIONS, Geriatric Use).

Pediatric: The pharmacokinetics of ENABLEX have not been studied in the pediatric population.

Gender: No dose adjustment is recommended based on gender. PK parameters were calculated for 22 male and 25 female healthy volunteers. Darifenacin Cmax and AUC at steady state were approximately 57%-79% and 61%-73% higher in females than in males, respectively.

Race: The effect of race on the pharmacokinetics of ENABLEX has not been characterized.

Renal Insufficiency: No dose adjustment is recommended for patients with renal impairment. A study of subjects with varying degrees of renal impairment (creatinine clearance between 10 and 136 mL/min) given ENABLEX 15 mg once daily to steady state demonstrated no clear relationship between renal function and darifenacin clearance.

Hepatic Insufficiency: The daily dose of ENABLEX should not exceed 7.5 mg once daily for patients with moderate hepatic impairment (Child Pugh B) (see PRECAUTIONS and DOSAGE AND ADMINISTRATION). No dose adjustment is recommended for patients with mild hepatic impairment (Child Pugh A).

ENABLEX pharmacokinetics were investigated in subjects with mild (Child Pugh A) or moderate (Child Pugh B) impairment of hepatic function given ENABLEX 15 mg once daily to steady state. Mild hepatic impairment had no effect on the pharmacokinetics of darifenacin. However, protein binding of darifenacin was affected by moderate hepatic impairment. After adjusting for plasma protein binding, unbound darifenacin exposure was estimated to be 4.7-fold higher in subjects with moderate hepatic impairment than subjects with normal hepatic function.

Subjects with severe hepatic impairment (Child Pugh C) have not been studied, therefore ENABLEX is not recommended for use in these patients (see PRECAUTIONS and DOSAGE AND ADMINISTRATION).

Drug-Drug Interactions

Effects of Other Drugs on Darifenacin

Darifenacin metabolism is primarily mediated by the cytochrome P450 enzymes CYP2D6 and CYP3A4. Therefore, inducers of CYP3A4 or inhibitors of either of these enzymes may alter darifenacin pharmacokinetics.

CYP2D6 Inhibitors: No dosing adjustments are recommended in the presence of CYP2D6 inhibitors. Darifenacin exposure following 30 mg once daily at steady state was 33% higher in the presence of the potent CYP2D6 inhibitor paroxetine 20 mg.

CYP3A4 Inhibitors: The daily dose of ENABLEX should not exceed 7.5 mg when coadministered with potent CYP3A4 inhibitors (e.g., ketoconazole, itraconazole, ritonavir, nelfinavir, clarithromycin and nefazodone) (see PRECAUTIONS and DOSAGE AND ADMINISTRATION). In a drug interaction study, when a 7.5 mg once-daily dose of ENABLEX was given to steady state and coadministered with the potent CYP3A4 inhibitor ketoconazole 400 mg, mean darifenacin Cmax increased to 11.2 ng/mL for EMs (n=10) and 55.4 ng/mL for one PM subject (n=1). Mean AUC increased to 143 and 939 ng.h/mL for EMs and for one PM subject, respectively. When a 15 mg daily dose of ENABLEX was given with ketoconazole, mean darifenacin Cmax increased to 67.6 ng/mL and 58.9 ng/mL for EMs (n=3) and one PM subject (n=1), respectively. Mean AUC increased to 1110 and 931 ng.h/mL for EMs and for one PM subject, respectively.

No dosing adjustments are recommended in the presence of moderate CYP3A4 inhibitors (e.g., erythromycin, fluconazole, diltiazem and verapamil). The mean Cmax and AUC of darifenacin following 30 mg once-daily dosing at steady state were 128% and 95% higher, respectively, in the presence of erythromycin. Coadministration of fluconazole and darifenacin 30 mg once daily at steady state increased darifenacin Cmax and AUC by 88% and 84%, respectively.

The mean Cmax and AUC of darifenacin following 30 mg once daily at steady state were 42% and 34% higher, respectively, in the presence of cimetidine, a mixed CYP P450 enzyme inhibitor.

Effects of Darifenacin on Other Drugs

In Vitro Studies: Based on in vitro human microsomal studies, ENABLEX is not expected to inhibit CYP1A2 or CYP2C9 at clinically relevant concentrations.

In Vivo Studies: The potential for clinical doses of ENABLEX to act as inhibitors of CYP2D6 or CYP3A4 substrates was investigated in specific drug interaction studies.

CYP2D6 Substrates: Caution should be taken when ENABLEX is used concomitantly with medications that are predominantly metabolized by CYP2D6 and which have a narrow therapeutic window, such as flecainide, thioridazine and tricyclic antidepressants (see PRECAUTIONS, Drug Interactions).

The mean Cmax and AUC of imipramine, a CYP2D6 substrate, were increased 57% and 70%, respectively, in the presence of steady-state darifenacin 30 mg once daily. This was accompanied by a 3.6-fold increase in the mean Cmax and AUC of desipramine, the active metabolite of imipramine.

CYP3A4 Substrates: Darifenacin (30 mg daily) coadministered with a single oral dose of midazolam 7.5 mg resulted in a 17% increase in midazolam exposure.

Darifenacin (10 mg t.i.d.) had no effect on the pharmacokinetics of the combination oral contraceptives containing levonorgestrel and ethinylestradiol.

Other Drugs: Darifenacin had no significant effect on prothrombin time when a single dose of warfarin 30 mg was coadministered with darifenacin (30 mg daily) at steady state. Standard therapeutic prothrombin time monitoring for warfarin should be continued.

Routine therapeutic drug monitoring for digoxin should be continued. Darifenacin (30 mg daily) coadministered with digoxin (0.25 mg) at steady state resulted in a 16% increase in digoxin exposure.

Electrophysiology

The effect of six-day treatment of 15-mg and 75-mg ENABLEX on QT/QTc interval was evaluated in a multiple-dose, double-blind, randomized, placebo- and active-controlled (moxifloxacin 400 mg) parallel-arm design study in 179 healthy adults (44% male, 56% female) aged 18 to 65. Subjects included 18% PMs and 82% EMs. The QT interval was measured over a 24-hour period both predosing and at steady state. The 75-mg ENABLEX dose was chosen because this achieves exposure similar to that observed in CYP2D6 poor metabolizers administered the highest recommended dose (15 mg) of darifenacin in the presence of a potent CYP3A4 inhibitor. At the doses studied, ENABLEX did not result in QT/QTc interval prolongation at any time during the steady state, while moxifloxacin treatment resulted in a mean increase from baseline QTcF of about 7.0 msec when compared to placebo. In this study, darifenacin 15-mg and 75-mg doses demonstrated a mean heart rate change of 3.1 and 1.3 bpm, respectively, when compared to placebo. However, in the Phase II/III clinical studies, the change in median HR following treatment with ENABLEX was no different from placebo.

CLINICAL STUDIES

ENABLEX® (darifenacin) extended-release tablets were evaluated for the treatment of patients with overactive bladder with symptoms of urgency, urge urinary incontinence, and increased urinary frequency in three randomized, fixed-dose, placebo-controlled, multicenter, double-blind, 12-week studies (Studies 1, 2 and 3) and one randomized, double-blind, placebo-controlled, multicenter, dose-titration study (Study 4). For study eligibility in all four studies, patients with symptoms of overactive bladder for at least six months were required to demonstrate at least eight micturitions and at least one episode of urinary urgency per day, and at least five episodes of urge urinary incontinence per week. The majority of patients were white (94%) and female (84%), with a mean age of 58 years, range 19 to 93 years. Thirty-three percent of patients were >65 years of age. These characteristics were well balanced across treatment groups. The study population was inclusive of both naïve patients who had not received prior pharmacotherapy for overactive bladder (60%) and those who had (40%).

Table 2 shows the efficacy data collected from 7- or 14-day voiding diaries in the three fixed-dose placebo-controlled studies of 1,059 patients treated with placebo, 7.5 mg or 15 mg once-daily ENABLEX for 12 weeks. A significant decrease in the primary endpoint, change from baseline in average weekly urge urinary incontinence episodes was observed in all three studies. Data is also shown for two secondary endpoints, change from baseline in the average number of micturitions per day (urinary frequency) and change from baseline in the average volume voided per micturition.

Table 2: Difference Between ENABLEX® (7.5 mg, 15 mg) and Placebo for the Week 12 Change from Baseline (Studies 1, 2 and 3)
 |  | Study 1 |  |  | Study 2 |  |  | Study 3
 |  | ENABLEX® 7.5 mg | ENABLEX® 15 mg | Placebo | ENABLEX® 7.5 mg | ENABLEX® 15 mg | Placebo | ENABLEX® 15 mg | Placebo
No. of Patients Entered |  | 229 | 115 | 164 | 108 | 107 | 109 | 112 | 115
Incontinence Episodes per Week
 | Median Baseline | 16.3 | 17.0 | 16.6 | 14.0 | 17.3 | 16.1 | 16.2 | 15.5
 | Median Change from Baseline | -9.0 | -10.4 | -7.6 | -8.1 | -10.4 | -5.9 | -11.4 | -9.0
 | Median Difference to Placebo | -1.5* | -2.1* | - | -2.8* | -4.3* | - | -2.4* | -
Micturitions per Day
 | Median Baseline | 10.1 | 10.1 | 10.1 | 10.3 | 11.0 | 10.1 | 10.5 | 10.4
 | Median Change from Baseline | -1.6 | -1.7 | -0.8 | -1.7 | -1.9 | -1.1 | -1.9 | -1.2
 | Median Difference to Placebo | -0.8* | -0.9* | - | -0.5 | -0.7* | - | -0.5 | -
Volume of Urine Passed per Void (mL)
 | Median Baseline | 160.2 | 151.8 | 162.4 | 161.7 | 157.3 | 162.2 | 155.0 | 147.1
 | Median Change from Baseline | 14.9 | 30.9 | 7.6 | 16.8 | 23.6 | 7.1 | 26.7 | 4.6
 | Median Difference to Placebo | 9.1* | 20.7* | - | 9.2 | 16.6* | - | 20.1* | -
* Indicates statistically significant difference versus placebo (p<0.05, Wilcoxon rank-sum test)

Table 3 shows the efficacy data from the dose-titration study in 395 patients who initially received 7.5-mg ENABLEX or placebo daily with the option to increase to 15-mg ENABLEX or placebo daily after two weeks.

Table 3: Difference Between ENABLEX® (7.5 mg/15 mg) and Placebo for the Week 12 Change from Baseline (Study 4)
 |  | ENABLEX® 7.5 mg /15 mg | Placebo
No. of Patients Treated |  | 268 | 127
Incontinence Episodes per Week
 | Median Baseline | 16.0 | 14.0
 | Median Change from Baseline | -8.2 | -6.0
 | Median Difference to Placebo | -1.4* | -
Micturitions per Day
 | Median Baseline | 9.9 | 10.4
 | Median Change from Baseline | -1.9 | -1.0
 | Median Difference to Placebo | -0.8* | -
Volume of Urine Passed per Void (mL)
 | Median Baseline | 173.7 | 177.2
 | Median Change from Baseline | 18.8 | 6.6
 | Median Difference to Placebo | 13.3 * | -
* Indicates statistically significant difference versus placebo (p<0.05, Wilcoxon rank-sum test)

As seen in Figures 2 a, b and c, reductions in the number of incontinence episodes per week were observed within the first two weeks in patients treated with ENABLEX 7.5 mg and 15 mg once daily compared to placebo. Further, these effects were sustained throughout the 12-week treatment period.

Figures 2 a,b,c. Median Change from Baseline at Weeks 2, 6, 12 for Number of Incontinence Episodes per Week (Studies 1, 2 and 3) Figure 2a, Study 1
Figure 2b, Study 2
Figure 2c, Study 3

INDICATIONS AND USAGE

ENABLEX® (darifenacin) extended-release tablets are indicated for the treatment of overactive bladder with symptoms of urge urinary incontinence, urgency and frequency.

CONTRAINDICATIONS

ENABLEX® (darifenacin) extended-release tablets are contraindicated in patients with urinary retention, gastric retention or uncontrolled narrow-angle glaucoma and in patients who are at risk for these conditions. ENABLEX is also contraindicated in patients with known hypersensitivity to the drug or its ingredients.

PRECAUTIONS

General

Risk of Urinary Retention

ENABLEX® (darifenacin) extended-release tablets should be administered with caution to patients with clinically significant bladder outflow obstruction because of the risk of urinary retention.

Decreased Gastrointestinal Motility

ENABLEX should be administered with caution to patients with gastrointestinal obstructive disorders because of the risk of gastric retention. ENABLEX, like other anticholinergic drugs, may decrease gastrointestinal motility and should be used with caution in patients with conditions such as severe constipation, ulcerative colitis, and myasthenia gravis.

Controlled Narrow-Angle Glaucoma

ENABLEX should be used with caution in patients being treated for narrow-angle glaucoma and only where the potential benefits outweigh the risks.

Patients with Hepatic Impairment

There are no dosing adjustments for patients with mild hepatic impairment. The daily dose of ENABLEX should not exceed 7.5 mg for patients with moderate hepatic impairment. ENABLEX has not been studied in patients with severe hepatic impairment and therefore is not recommended for use in this patient population (see CLINICAL PHARMACOLOGY, Pharmacokinetics in Special Populations and DOSAGE AND ADMINISTRATION).

Information for Patients

Patients should be informed that anticholinergic agents, such as ENABLEX, may produce clinically significant adverse effects related to anticholinergic pharmacological activity including constipation, urinary retention and blurred vision. Heat prostration (due to decreased sweating) can occur when anticholinergics such as ENABLEX are used in a hot environment. Because anticholinergics, such as ENABLEX, may produce dizziness or blurred vision, patients should be advised to exercise caution in decisions to engage in potentially dangerous activities until the drug’s effects have been determined. Patients should read the patient information leaflet before starting therapy with ENABLEX.

ENABLEX extended-release tablets should be taken once daily with liquid. They may be taken with or without food, and should be swallowed whole and not chewed, divided or crushed.

Drug Interactions

The daily dose of ENABLEX should not exceed 7.5 mg when coadministered with potent CYP3A4 inhibitors (e.g., ketoconazole, itraconazole, ritonavir, nelfinavir, clarithromycin and nefazadone) (see CLINICAL PHARMACOLOGY and DOSAGE AND ADMINISTRATION).

Caution should be taken when ENABLEX is used concomitantly with medications that are predominantly metabolized by CYP2D6 and which have a narrow therapeutic window, such as flecainide, thioridazine and tricyclic antidepressants (see CLINICAL PHARMACOLOGY).

The concomitant use of ENABLEX with other anticholinergic agents may increase the frequency and/or severity of dry mouth, constipation, blurred vision and other anticholinergic pharmacological effects. Anticholinergic agents may potentially alter the absorption of some concomitantly administered drugs due to effects on gastrointestinal motility.

Drug Laboratory Test Interactions

Interactions between darifenacin and laboratory tests have not been studied.

Carcinogenesis/Mutagenesis/Impairment of Fertility

Carcinogenicity studies with darifenacin were conducted in mice and rats. No evidence of drug-related carcinogenicity was revealed in a 24-month study in mice at dietary doses up to 100 mg/kg/day or approximately 32 times the estimated human-free AUC0-24h reached with 15 mg, the maximum recommended human dose (AUC at MRHD) and in a 24-month study in rats at doses up to 15 mg/kg/day or up to approximately 12 times the AUC at MRHD in female rats and approximately eight times the AUC at MRHD in male rats.

Darifenacin was not mutagenic in the bacterial mutation assays (Ames test) and the Chinese hamster ovary assay, and not clastogenic in the human lymphocyte assay, and the in vivo mouse bone marrow cytogenetics assay.

There was no evidence for effects on fertility in male or female rats treated at oral doses up to 50 mg/kg/day. Exposures in this study correspond to approximately 78 times the AUC at MRHD.

Pregnancy Category C

Darifenacin was not teratogenic in rats and rabbits at doses up to 50 and 30 mg/kg/day, respectively. At the dose of 50 mg/kg in rats, there was a delay in the ossification of the sacral and caudal vertebrae which was not observed at 10 mg/kg (approximately 13 times the AUC of free plasma concentration at MRHD). Exposure in this study at 50 mg/kg corresponds to approximately 59 times the AUC of free plasma concentration at MRHD. Dystocia was observed in dams at 10 mg/kg/day (17 times the AUC of free plasma concentration at MRHD). Slight developmental delays were observed in pups at this dose. At 3 mg/kg/day (five times the AUC of free plasma concentration at MRHD) there were no effects on dams or pups. At the dose of 30 mg/kg in rabbits, darifenacin was shown to increase postimplantation loss but not at 10 mg/kg (nine times the AUC of free plasma concentration at MRHD). Exposure to unbound drug at 30 mg/kg in this study corresponds to approximately 28 times the AUC at MRHD. In rabbits, dilated ureter and/or kidney pelvis was observed in offspring at 30 mg/kg/day and one case was observed at 10 mg/kg/day along with urinary bladder dilation consistent with pharmacological action of darifenacin. No effect was observed at 3 mg/kg/day (2.8 times the AUC of free plasma concentration at MRHD). There are no studies of darifenacin in pregnant women. Because animal reproduction studies are not always predictive of human response, ENABLEX should be used during pregnancy only if the benefit to the mother outweighs the potential risk to the fetus.

Nursing Mothers

Darifenacin is excreted into the milk of rats. It is not known whether darifenacin is excreted into human milk and therefore caution should be exercised before ENABLEX is administered to a nursing woman.

Pediatric Use

The safety and effectiveness of ENABLEX in pediatric patients have not been established.

Geriatric Use

In the Phase III fixed-dose, placebo-controlled, clinical studies, 30% of patients treated with ENABLEX were over 65 years of age. No overall differences in safety or efficacy were observed between these patients (n=207) and younger patients <65 years (n=464). No dose adjustment is recommended for elderly patients (see CLINICAL PHARMACOLOGY, Pharmacokinetics in Special Populations and CLINICAL STUDIES).

ADVERSE REACTIONS

During the clinical development of ENABLEX® (darifenacin) extended-release tablets, a total of 7,363 patients and volunteers were treated with doses of darifenacin from 3.75 mg to 75 mg once daily.

The safety of ENABLEX was evaluated in Phase II and III controlled clinical trials in a total of 8,830 patients, 6,001 of whom were treated with ENABLEX. Of this total, 1,069 patients participated in three, 12-week, Phase III, fixed-dose efficacy and safety studies. Of this total, 337 and 334 patients received ENABLEX 7.5 mg daily and 15 mg daily, respectively. In all long-term trials combined, 1,216 and 672 patients received treatment with ENABLEX for at least 24 and 52 weeks, respectively.

In all placebo-controlled trials combined, the incidence of serious adverse events for 7.5 mg, 15 mg and placebo was similar.

In all fixed-dose Phase III studies combined, 3.3% of patients treated with ENABLEX discontinued due to all adverse events versus 2.6% in placebo. Dry mouth leading to study discontinuation occurred in 0%, 0.9%, and 0% of patients treated with ENABLEX 7.5 mg daily, ENABLEX 15 mg daily and placebo, respectively. Constipation leading to study discontinuation occurred in 0.6%, 1.2%, and 0.3% of patients treated with ENABLEX 7.5 mg daily, ENABLEX 15 mg daily and placebo, respectively.

Table 4 lists the adverse events reported (regardless of causality) in 2% or more of patients treated with 7.5-mg or 15-mg ENABLEX extended-release tablets and greater than placebo in the three, fixed-dose, placebo-controlled Phase III studies (Studies 1, 2 and 3). Adverse events were reported by 54% and 66% of patients receiving 7.5 mg and 15 mg once-daily ENABLEX extended-release tablets, respectively, and by 49% of patients receiving placebo. In these studies, the most frequently reported adverse events were dry mouth and constipation. The majority of adverse events in ENABLEX-treated subjects were mild or moderate in severity and most occurred during the first two weeks of treatment.

Table 4: Incidence of Adverse Events* Reported in ≥2.0% of Patients Treated with ENABLEX® Extended-Release Tablets and More Frequent with ENABLEX® than with Placebo in Three, Fixed-Dose, Placebo-Controlled, Phase III Studies (Studies 1, 2, and 3)
Body System | Adverse Event | Percentage of Subjects with Adverse Event (%)
 |  | ENABLEX® 7.5 mg N=337 | ENABLEX® 15 mg N=334 | Placebo N=388
Digestive | Dry Mouth Constipation Dyspepsia Abdominal Pain Nausea Diarrhea | 20.2 14.8 2.7 2.4 2.7 2.1 | 35.3 21.3 8.4 3.9 1.5 0.9 | 8.2 6.2 2.6 0.5 1.5 1.8
Urogenital | Urinary Tract Infection | 4.7 | 4.5 | 2.6
Nervous | Dizziness | 0.9 | 2.1 | 1.3
Body as a Whole | Asthenia | 1.5 | 2.7 | 1.3
Eye | Dry Eyes | 1.5 | 2.1 | 0.5
*Regardless of causality

Other adverse events reported, regardless of causality, by ≥1% of ENABLEX patients in either the 7.5 mg or 15 mg once-daily darifenacin-dose groups in these fixed-dose, placebo-controlled Phase III studies include: abnormal vision, accidental injury, back pain, dry skin, flu syndrome, pain, hypertension, vomiting, peripheral edema, weight gain, arthralgia, bronchitis, pharyngitis, rhinitis, sinusitis, rash, pruritus, urinary tract disorder and vaginitis.

Study 4 was a 12-week, placebo-controlled, dose-titration regimen study in which ENABLEX was administered in accordance with dosing recommendations (see DOSAGE AND ADMINISTRATION). All patients initially received placebo or ENABLEX 7.5 mg daily, and after two weeks, patients and physicians were allowed to adjust upward to ENABLEX 15 mg if needed. In this study, the most commonly reported adverse events were also constipation and dry mouth. The incidence of discontinuation due to all adverse events was 3.1% and 6.7% for placebo and for ENABLEX, respectively. Table 5 lists the adverse events (regardless of causality) reported in >3% of patients treated with ENABLEX extended-release tablets and greater than placebo.

Table 5: Number (%) of Adverse Events* Reported in >3% of Patients Treated with ENABLEX® Extended-Release Tablets, and More Frequent with ENABLEX® than Placebo, in the Placebo-Controlled, Dose-Titration, Phase III Study (Study 4)
Adverse Event | ENABLEX® 7.5 mg/15 mg N=268 | Placebo N=127
Constipation Dry Mouth Headache Dyspepsia Nausea Urinary Tract Infection Accidental Injury Flu Syndrome | 56 (20.9%) 50 (18.7%) 18 (6.7%) 12 (4.5%) 11 (4.1%) 10 (3.7%) 8 (3.0%) 8 (3.0%) | 10 (7.9%) 11 (8.7%) 7 (5.5%) 2 (1.6%) 2 (1.6%) 4 (3.1%) 3 (2.4%) 3 (2.4%)
*Regardless of causality

Acute urinary retention (AUR) requiring treatment was reported in a total of 16 patients in the ENABLEX Phase I-III clinical trials. Of these 16 cases, seven were reported as serious adverse events, including one patient with detrusor hyperreflexia secondary to a stroke, one patient with benign prostatic hypertrophy (BPH), one patient with irritable bowel syndrome (IBS) and four overactive bladder (OAB) patients taking darifenacin 30 mg daily. Of the remaining nine cases, none were reported as serious adverse events. Three occurred in OAB patients taking the recommended doses, and two of these required bladder catheterization for 1-2 days.

Constipation was reported as a serious adverse event in six patients in the ENABLEX Phase I-III clinical trials, including one patient with benign prostatic hypertrophy (BPH), one OAB patient taking darifenacin 30 mg daily, and only one OAB patient taking the recommended doses. The latter patient was hospitalized for investigation with colonoscopy after reporting nine months of chronic constipation that was reported as being moderate in severity.

Postmarketing Experience

The following events have been reported in association with darifenacin use in worldwide postmarketing experience. Because these spontaneously reported events are from the worldwide postmarketing experience, the frequency of events and the role of darifenacin in their causation cannot be reliably determined.

General: hypersensitivity reactions, including angioedema.

Central Nervous: confusion and hallucinations.

Cardiovascular: palpitations

OVERDOSAGE

Overdosage with antimuscarinic agents, including ENABLEX® (darifenacin) extended-release tablets, can result in severe antimuscarinic effects. Treatment should be symptomatic and supportive. In the event of overdosage, ECG monitoring is recommended. ENABLEX has been administered in clinical trials at doses up to 75 mg (five times the maximum therapeutic dose) and signs of overdose were limited to abnormal vision.

DOSAGE AND ADMINISTRATION

The recommended starting dose of ENABLEX® (darifenacin) extended-release tablets is 7.5 mg once daily. Based upon individual response, the dose may be increased to 15 mg once daily, as early as two weeks after starting therapy.

ENABLEX extended-release tablets should be taken once daily with liquid. They may be taken with or without food, and should be swallowed whole and not chewed, divided or crushed.

For patients with moderate hepatic impairment or when coadministered with potent CYP3A4 inhibitors (e.g., ketoconazole, itraconazole, ritonavir, nelfinavir, clarithromycin and nefazadone), the daily dose of ENABLEX should not exceed 7.5 mg. ENABLEX is not recommended for use in patients with severe hepatic impairment (see CLINICAL PHARMACOLOGY and PRECAUTIONS).

HOW SUPPLIED

ENABLEX® 7.5 mg extended-release tablets are round, shallow, convex, white-colored tablets, and are identified with “DF” on one side and “7.5” on the reverse.

Bottle of 30 NDC 54868-5704-0

ENABLEX® 15 mg extended-release tablets are round, shallow, convex, light peach-colored tablets, and are identified with “DF” on one side and “15” on the reverse.

Bottle of 30 NDC 54868-5363-0

Storage

Store at 25°C (77°F); excursions permitted to 15-30°C (59-86°F) [see USP Controlled Room Temperature]. Protect from light.

Keep this and all drugs out of the reach of children.

REV: January 2010 T2010-04

INFORMATION FOR PATIENTS

ENABLEX® (ěn-ā-blěx)

(darifenacin)

Extended-release tablets

7.5 mg or 15 mg

Rx only

Read the Patient Information that comes with ENABLEX® before you start taking it and each time you get a refill. There may be new information. This leaflet does not take the place of talking to your doctor or other healthcare professional about your medical condition or your treatment. Only your doctor or healthcare professional can determine if treatment with ENABLEX is right for you.

What is ENABLEX?

ENABLEX is a prescription medicine used in adults to treat the following symptoms due to a condition called overactive bladder:

- having a strong need to go to the bathroom right away (also called “urgency”)
- leaking or wetting accidents (also called “urinary incontinence”)
- having to go to the bathroom too often (also called “urinary frequency”)

What is overactive bladder?

Overactive bladder happens when you cannot control your bladder contractions. When these muscle contractions happen too often or cannot be controlled, you get symptoms of overactive bladder, which are urinary urgency, urinary incontinence (leakage) and urinary frequency.

Who should not take ENABLEX?

Do not take ENABLEX if you:

- are not able to empty your bladder (also called “urinary retention”)
- have delayed or slow emptying of your stomach (also called “gastric retention”)
- have an eye problem called “uncontrolled narrow-angle glaucoma”
- are allergic to ENABLEX or to any of its ingredients. See the end of this leaflet for a complete list of ingredients.

ENABLEX has not been studied in children.

What should I tell my doctor before starting ENABLEX?

Before starting ENABLEX, tell your doctor or healthcare professional about all of your medical conditions including if you:

- have any stomach or intestinal problems, or problems with constipation
- have trouble emptying your bladder or if you have a weak urine stream
- have an eye problem called narrow-angle glaucoma
- have liver problems
- are pregnant or are planning to become pregnant. It is not known if ENABLEX can harm your unborn baby.
- are breast-feeding. It is not known if ENABLEX passes into breast milk and if it can harm your baby.

Tell your doctor about all the medicines you take, including prescription and nonprescription medicines, vitamins, and herbal supplements. ENABLEX and certain other medicines can interact with each other, causing side effects. Especially tell your doctor if you take:

- ketoconazole (Nizoral®) or itraconazole (Sporanox®), antifungal medicines
- clarithromycin (Biaxin®), an antibiotic medicine
- ritonivir or nelfinavir (Viracept®), antiviral medicines
- nefazadone (Serzone®), a depression medicine
- flecainide (Tambocor™), an abnormal heartbeat (antiarrhythmia) medicine
- thioridazine (Mellaril®), a mental disorder (antipsychotic) medicine
- a medicine called a tricyclic antidepressant

Know all the medicines you take. Keep a list of them with you to show your doctor and pharmacist each time you get a new medicine.

How should I take ENABLEX?

Take ENABLEX exactly as prescribed. Your doctor will prescribe the dose that is right for you. Your doctor may prescribe the lowest dose if you have certain medical conditions such as liver problems.

- You should take ENABLEX once daily with liquid.
- ENABLEX should be swallowed whole and not chewed, divided or crushed.
- ENABLEX may be taken with or without food.
- If you miss a dose of ENABLEX, begin taking ENABLEX again the next day. Do not take two doses of ENABLEX in the same day.
- If you take too much ENABLEX, call your local Poison Control Center or emergency room right away.

What are the possible side effects of ENABLEX?

The most common side effects with ENABLEX are:

- dry mouth
- constipation

ENABLEX may cause other less common side effects that include:

- blurred vision. Use caution while driving or doing dangerous activities until you know how ENABLEX affects you.
- heat prostration. Heat prostration (due to decreased sweating) can occur when drugs such as ENABLEX are used in a hot environment.

These are not all the side effects with ENABLEX. For more information, ask your doctor, healthcare professional or pharmacist.

How do I store ENABLEX?

- Keep ENABLEX and all medicines out of the reach of children.
- Store ENABLEX at room temperature, 59 to 86ºF (15 to 30ºC). Protect from light.
- Safely dispose of ENABLEX that is out of date or no longer needed.

General information about ENABLEX

Medicines are sometimes prescribed for conditions that are not mentioned in patient information leaflets. Do not give ENABLEX to other people, even if they have the same symptoms you have. It may harm them.

This leaflet summarizes the most important information about ENABLEX. If you would like more information, talk with your doctor. You can ask your pharmacist or doctor for information about ENABLEX that is written for health professionals. You can also call the product information department at 1-888-44-ENABLEX (1-888-443-6225) or visit the website at www.Enablex.com.

What are the ingredients in ENABLEX?

Active Ingredient: darifenacin

Inactive Ingredients: dibasic calcium phosphate, hypromellose (hydroxypropyl methylcellulose), magnesium stearate, polyethylene glycol, talc, titanium dioxide. The 15 mg tablet also contains iron oxide red and iron oxide yellow.

Appearance:

The 7.5-mg tablet is round and white-colored with “DF” on one side and “7.5” on the other side.

The 15-mg tablet is round and peach-colored with “DF” on one side and “15” on the other side.

* Mellaril® is a registered trademark of Novartis. The other brands listed are the trademarks of their respective owners and are not trademarks of Novartis.

REV: JANUARY 2010 T2010-05

Manufactured by:

Novartis Pharma Stein AG,

Stein, Switzerland

Distributed by:

Novartis Pharmaceuticals Corporation

East Hanover, New Jersey 07936

Marketed with:

Warner Chilcott Pharmaceuticals Inc.

Mason, Ohio 45040

© Novartis

Relabeling of "Additional Barcode" label by:
Physicians Total Care, Inc.
Tulsa, OK 74146

PRINCIPAL DISPLAY PANEL

Package Label – 7.5 mg per tablet

Rx Only

Enablex® (darifenacin)

Extended-release tablets

PRINCIPAL DISPLAY PANEL

Package Label – 15 mg per tablet

Rx Only

Enablex® (darifenacin)

Extended-release tablets